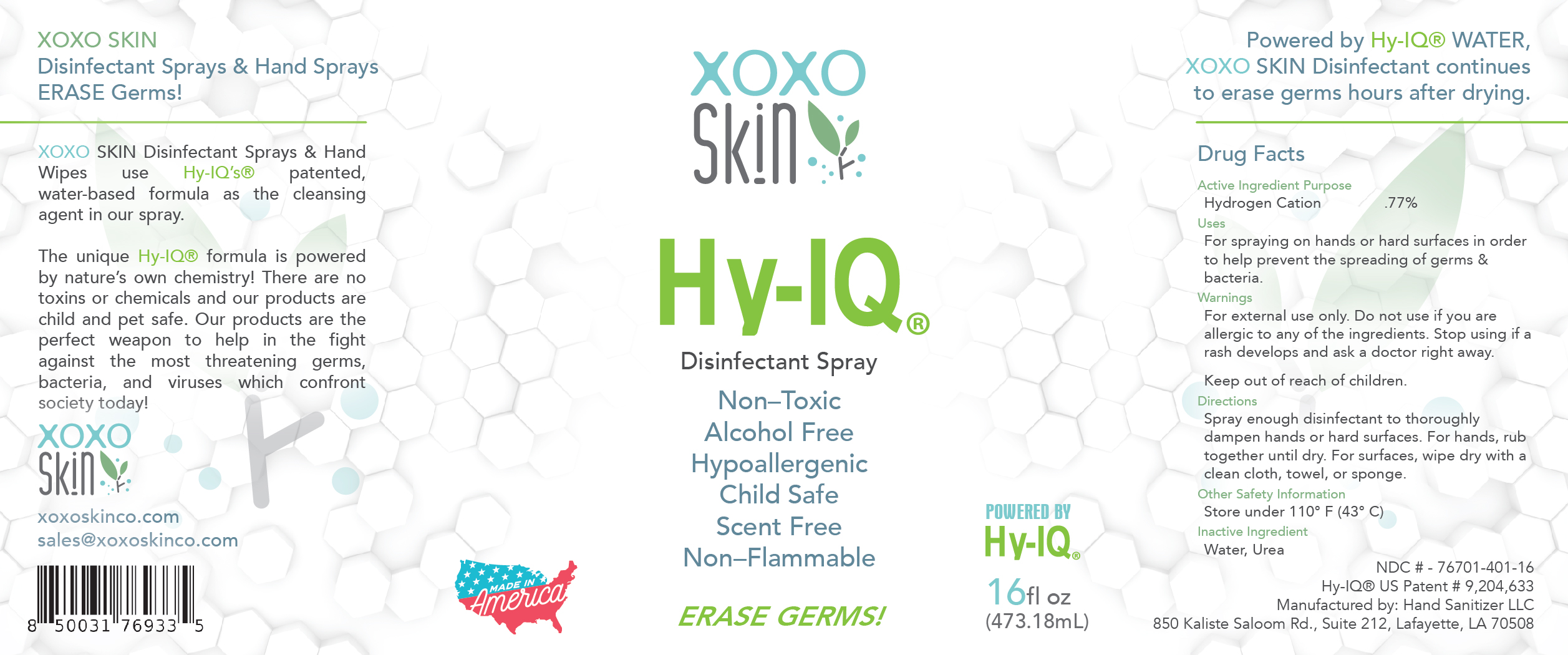 DRUG LABEL: XOXO Disinfectant
NDC: 76701-401 | Form: SPRAY
Manufacturer: Hand Sanitizer LLC
Category: otc | Type: HUMAN OTC DRUG LABEL
Date: 20210911

ACTIVE INGREDIENTS: HYDROGEN CATION 10 mg/1 mL
INACTIVE INGREDIENTS: UREA 50 mg/1 mL; WATER 940 mg/1 mL

XOXO Disinfectant

Active Ingredient

Hydrogen Cation .77%

Purpose

Antiseptic

Uses

For spraying on hands or hard surfaces in order to help prevent the spreading of germs and bacteria.

Warnings

For external use only. Do not use if you are allergic to any of the ingredients. Stop using if a rash develops and ask a doctor right away.

Keep Out of Reach of Children

Directions

Spray enough XOXO Skin Disinfectant Spray to thoroughly dampen hands or hard surfaces. For hands, rub together until dry. For surfaces, wipe dry with a clean cloth, towel, or sponge.

Other Safety Information

Store under 110º F (43º C)

Inactive Ingredient

Water, Urea

XOXO DISINFECTANT SPRAY